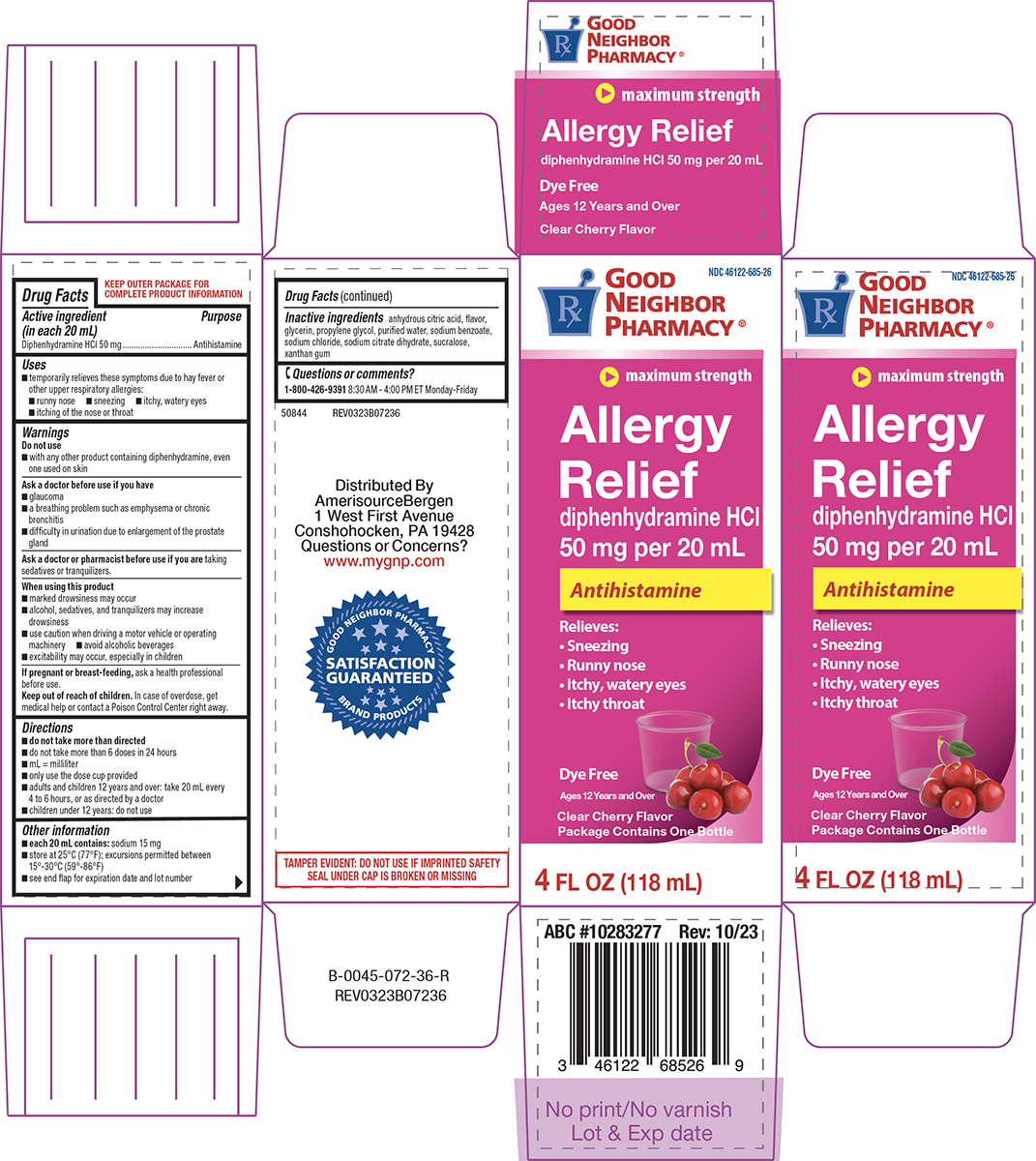 DRUG LABEL: Allergy Relief
NDC: 46122-685 | Form: SOLUTION
Manufacturer: Amerisource Bergen
Category: otc | Type: HUMAN OTC DRUG LABEL
Date: 20260106

ACTIVE INGREDIENTS: DIPHENHYDRAMINE HYDROCHLORIDE 50 mg/20 mL
INACTIVE INGREDIENTS: ANHYDROUS CITRIC ACID; GLYCERIN; PROPYLENE GLYCOL; WATER; SODIUM BENZOATE; SODIUM CHLORIDE; TRISODIUM CITRATE DIHYDRATE; SUCRALOSE; XANTHAN GUM

Good Neighbor Pharmacy 44-072

Active ingredient (in each 20 mL)

Diphenhydramine HCl 50 mg

Purpose

Antihistamine

Uses

- temporarily relieves these symptoms due to hay fever or other upper respiratory allergies:
  - runny nose
  - sneezing
  - itchy, watery eyes
  - itching of the nose or throat

Warnings

Do not use

- with any other product containing diphenhydramine, even one used on skin

Ask a doctor before use if you have

- glaucoma
- a breathing problem such as emphysema or chronic bronchitis
- difficulty in urination due to enlargement of the prostate gland

Ask a doctor or pharmacist before use if you are

taking sedatives or tranquilizers.

When using this product

- marked drowsiness may occur
- alcohol, sedatives, and tranquilizers may increase drowsiness
- use caution when driving a motor vehicle or operating machinery
- avoid alcoholic beverages
- excitability may occur, especially in children

If pregnant or breast-feeding,

ask a health professional before use.

Keep out of reach of children.

In case of overdose, get medical help or contact a Poison Control Center right away.

Directions

- do not take more than directed
- do not take more than 6 doses in 24 hours
- mL = milliliter
- only use the dose cup provided
- adults and children 12 years and over: take 20 mL every 4 to 6 hours, or as directed by a doctor
- children under 12 years: do not use

Other information

- each 20 mL contains: sodium 15 mg
- store at 25°C (77°F); excursions permitted between 15°-30°C (59°-86°F)
- see end flap for expiration date and lot number

Inactive ingredients

anhydrous citric acid, flavor, glycerin, propylene glycol, purified water, sodium benzoate, sodium chloride, sodium citrate dihydrate, sucralose, xanthan gum

Questions or comments?

1-800-426-9391 8:30 AM - 4:00 PM ET Monday-Friday

Principal display panel

NDC 46122-685-26

GOOD
NEIGHBOR
PHARMACY®

maximum strength

Allergy
Relief
diphenhydramine HCl
50 mg per 20 mL
Antihistamine

Relieves:
• Sneezing
• Runny nose
• Itchy, watery eyes
• Itchy throat

Dye Free

Clear Cherry Flavor
Package Contains One Bottle

4 FL OZ (118 mL)

TAMPER EVIDENT: DO NOT USE IF IMPRINTED SAFETY
SEAL UNDER CAP IS BROKEN OR MISSING

50844 REV0323B07236

Distributed By
AmerisourceBergen
1 West First Avenue
Conshohocken, PA 19428
Questions or Concerns?
www.mygnp.com

ABC #10283277 Rev: 10/23

Good Neighbor 44-072